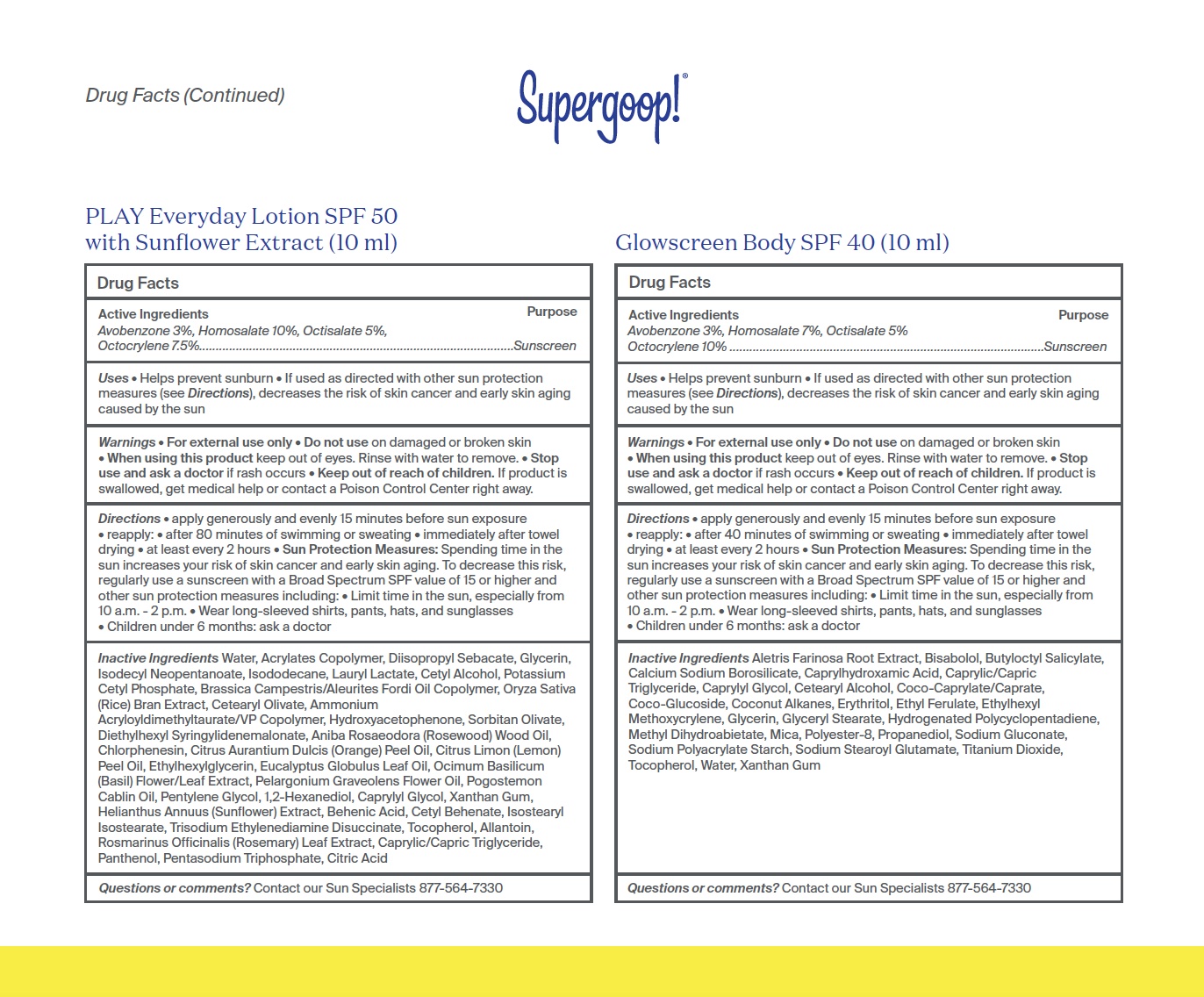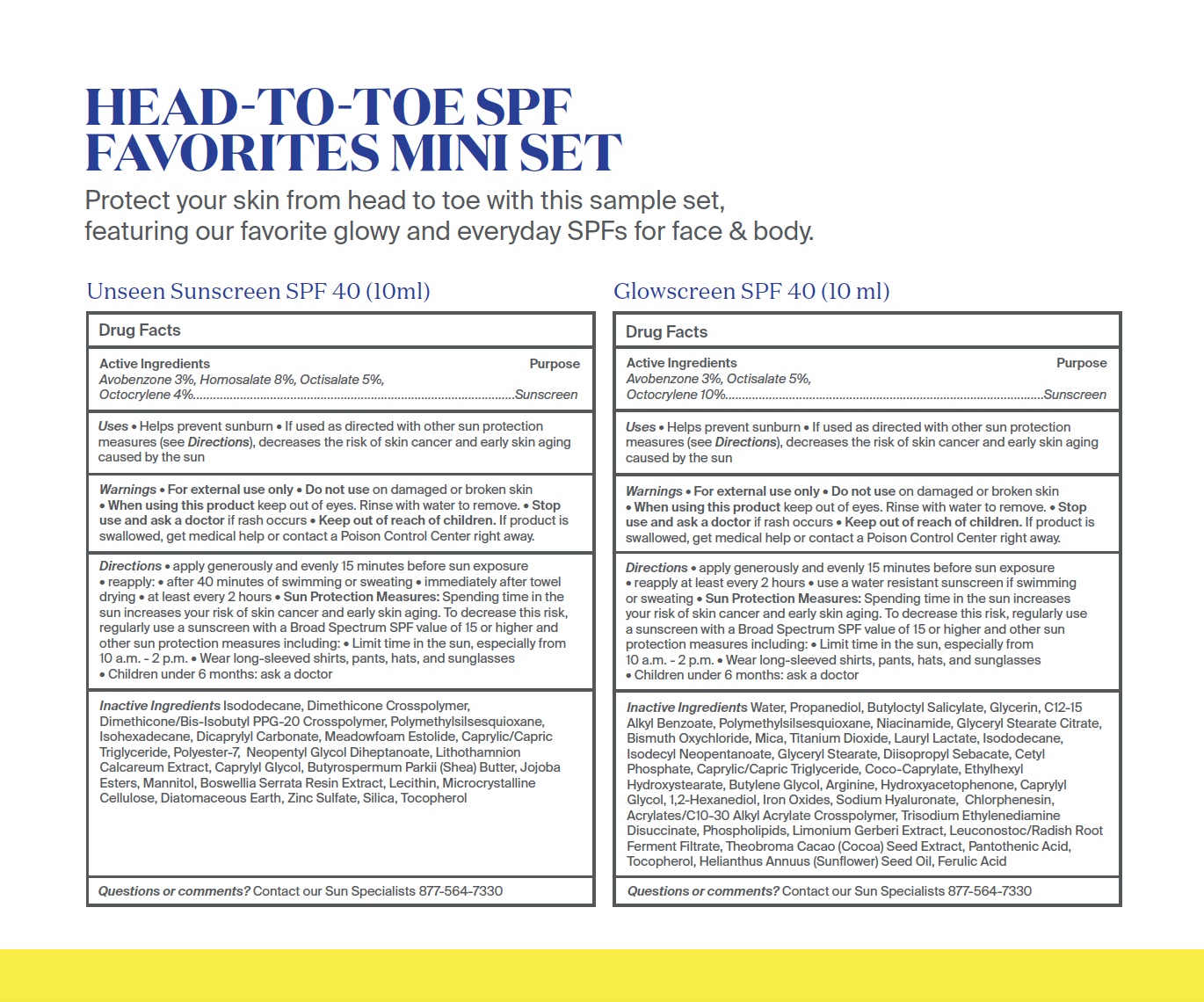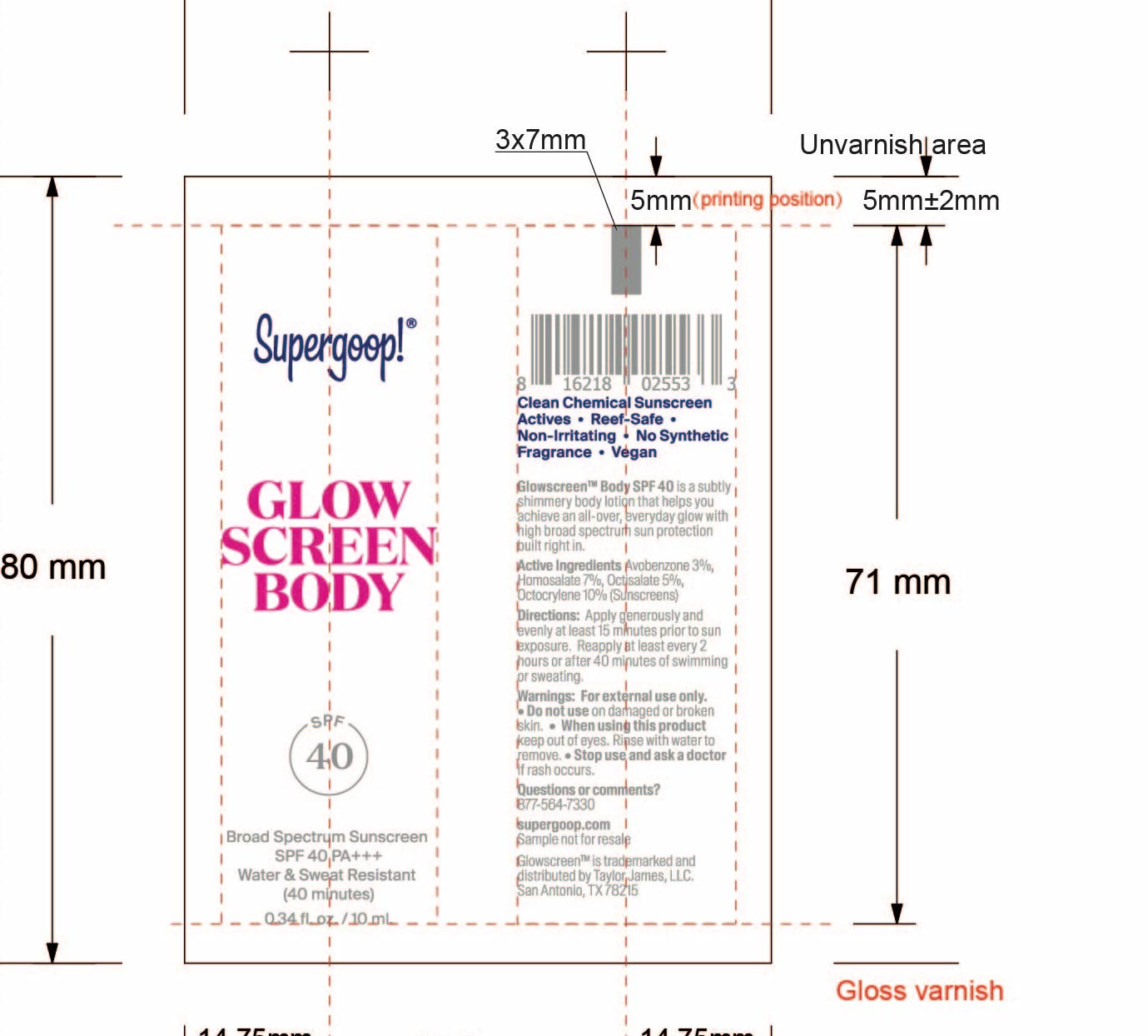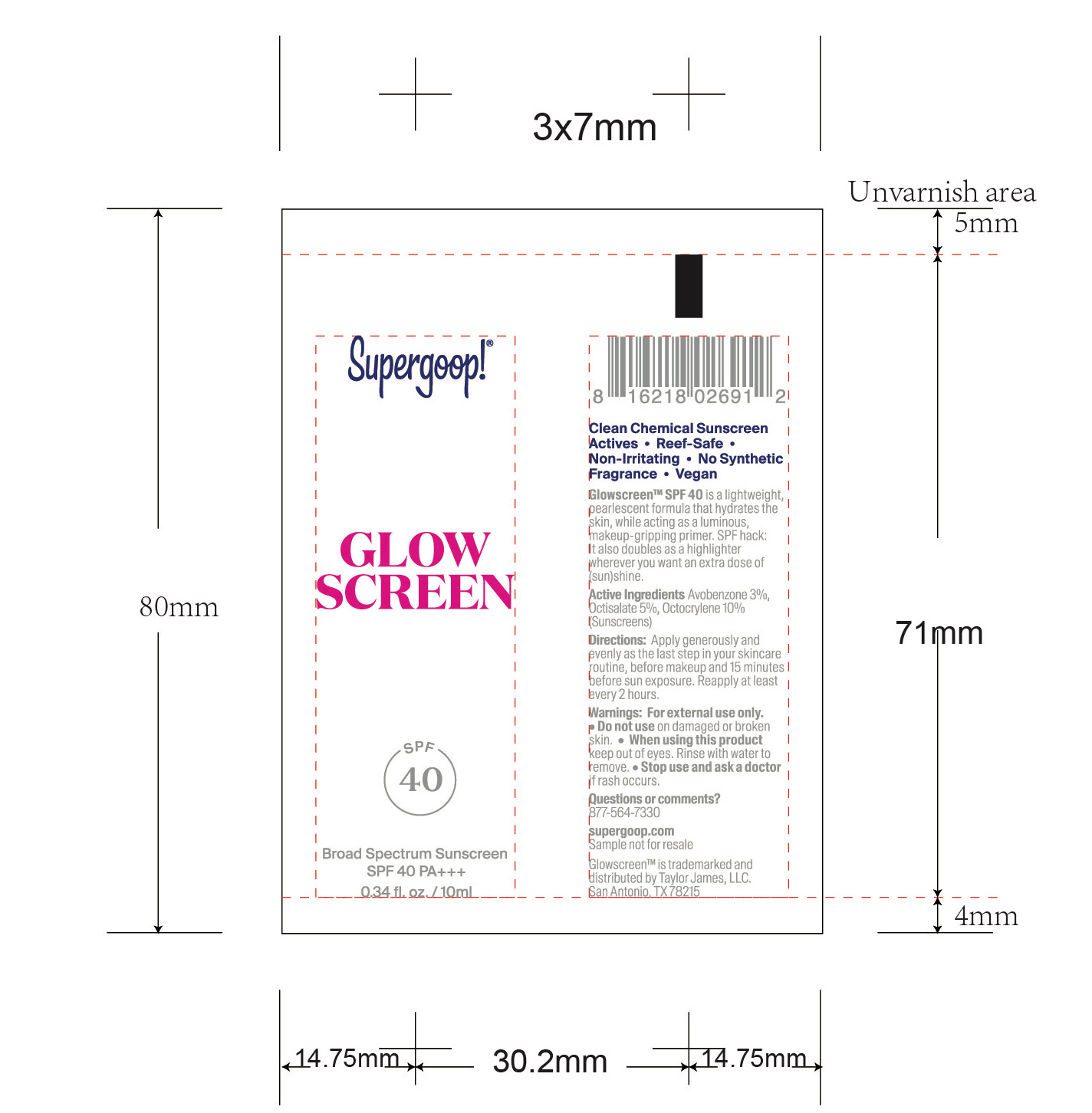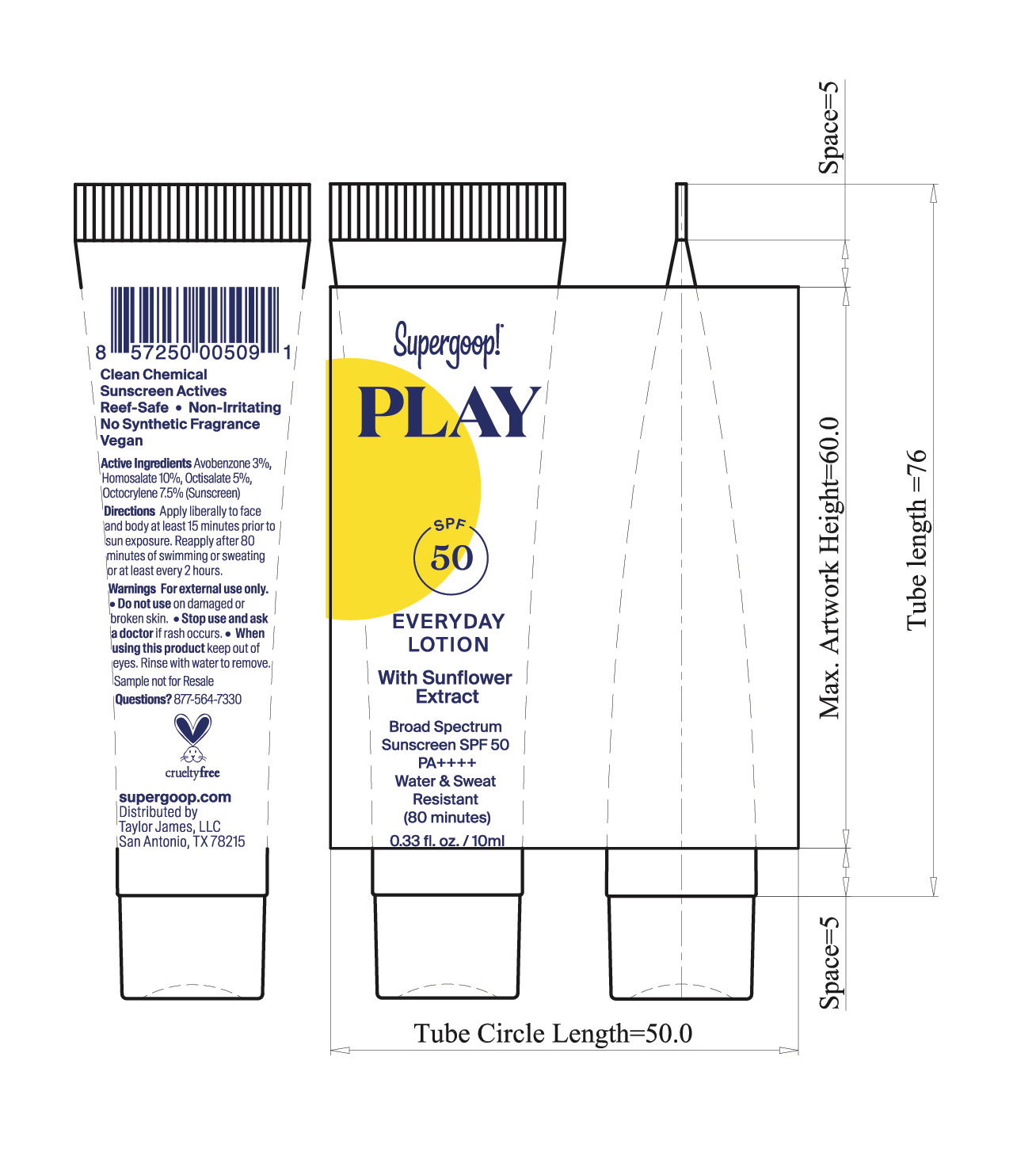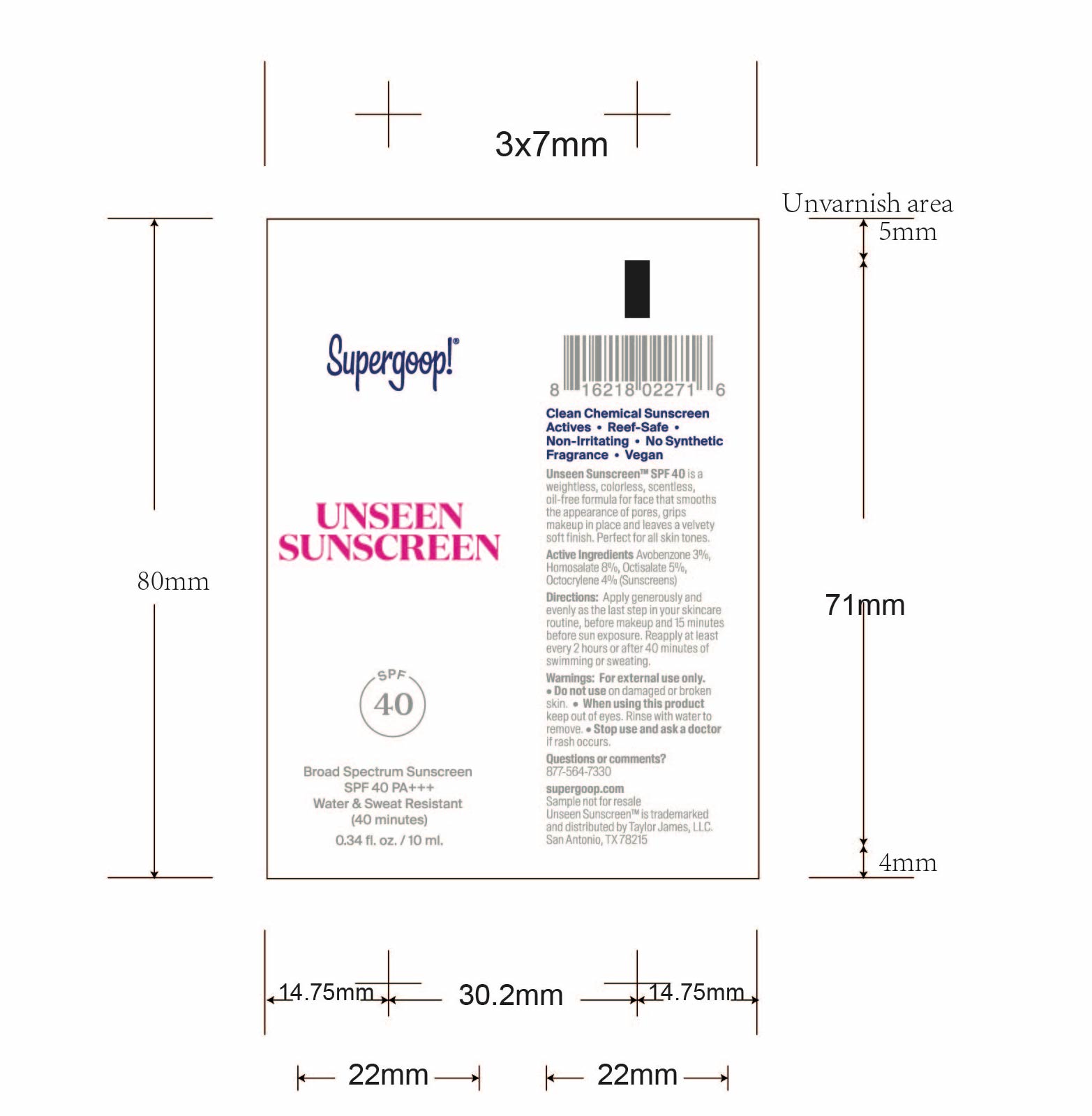 DRUG LABEL: Head-to-Toe Favorites Mini Set
NDC: 82384-0025 | Form: KIT | Route: TOPICAL
Manufacturer: System Beauty, LLC
Category: otc | Type: HUMAN OTC DRUG LABEL
Date: 20211209

ACTIVE INGREDIENTS: HOMOSALATE 10 g/100 mL; OCTOCRYLENE 7.5 g/100 mL; AVOBENZONE 3 g/100 mL; OCTISALATE 5 g/100 mL; AVOBENZONE 3 g/100 mL; HOMOSALATE 7 g/100 mL; OCTOCRYLENE 10 g/100 mL; OCTISALATE 5 g/100 mL; HOMOSALATE 8 g/100 mL; OCTISALATE 5 g/100 mL; AVOBENZONE 3 g/100 mL; OCTOCRYLENE 4 g/100 mL; OCTOCRYLENE 10 g/100 mL; AVOBENZONE 3 g/100 mL; OCTISALATE 5 g/100 mL
INACTIVE INGREDIENTS: LAURYL LACTATE; SORBITAN OLIVATE; ROSEWOOD OIL; ORANGE OIL, COLD PRESSED; CHLORPHENESIN; BEHENIC ACID; PANTHENOL; CITRIC ACID MONOHYDRATE; ROSEMARY; MEDIUM-CHAIN TRIGLYCERIDES; SODIUM TRIPOLYPHOSPHATE ANHYDROUS; PENTYLENE GLYCOL; LEMON OIL, COLD PRESSED; OCIMUM BASILICUM FLOWERING TOP; PELARGONIUM GRAVEOLENS FLOWER OIL; 1,2-HEXANEDIOL; DIETHYLHEXYL SYRINGYLIDENEMALONATE; ETHYLHEXYLGLYCERIN; EUCALYPTUS OIL; POGOSTEMON CABLIN LEAF OIL; RICE BRAN; CETYL ALCOHOL; AMMONIUM ACRYLOYLDIMETHYLTAURATE/VP COPOLYMER; HYDROXYACETOPHENONE; ISODECYL NEOPENTANOATE; POTASSIUM CETYL PHOSPHATE; CETEARYL OLIVATE; GLYCERIN; ISODODECANE; DIISOPROPYL SEBACATE; TRISODIUM ETHYLENEDIAMINE DISUCCINATE; TOCOPHEROL; ALLANTOIN; CAPRYLYL GLYCOL; XANTHAN GUM; HELIANTHUS ANNUUS FLOWERING TOP; ISOSTEARYL ISOSTEARATE; CETYL BEHENATE; WATER; PROPANEDIOL; TITANIUM DIOXIDE; COCONUT ALKANES; MEDIUM-CHAIN TRIGLYCERIDES; CAPRYLYL GLYCOL; GLYCERYL MONOSTEARATE; METHYL DIHYDROABIETATE; ERYTHRITOL; CAPRYLHYDROXAMIC ACID; SODIUM GLUCONATE; SODIUM STEAROYL GLUTAMATE; CETOSTEARYL ALCOHOL; ETHYL FERULATE; GLYCERIN; XANTHAN GUM; COCO GLUCOSIDE; COCOYL CAPRYLOCAPRATE; MICA; POLYESTER-8 (1400 MW, CYANODIPHENYLPROPENOYL CAPPED); BUTYLOCTYL SALICYLATE; ETHYLHEXYL METHOXYCRYLENE; ALETRIS FARINOSA ROOT; LEVOMENOL; TOCOPHEROL; WATER; CAPRYLYL GLYCOL; SHEA BUTTER; SILICON DIOXIDE; TOCOPHEROL; MICROCRYSTALLINE CELLULOSE; DIATOMACEOUS EARTH; MANNITOL; POLYMETHYLSILSESQUIOXANE (11 MICRONS); DICAPRYLYL CARBONATE; POLYESTER-7; DIMETHICONE/BIS-ISOBUTYL PPG-20 CROSSPOLYMER; INDIAN FRANKINCENSE; ZINC SULFATE; ISODODECANE; DIMETHICONE CROSSPOLYMER (450000 MPA.S AT 12% IN CYCLOPENTASILOXANE); MEDIUM-CHAIN TRIGLYCERIDES; PHYMATOLITHON CALCAREUM; NEOPENTYL GLYCOL DIHEPTANOATE; LECITHIN, SUNFLOWER; ISOHEXADECANE; LAURYL LACTATE; CETYL PHOSPHATE; MEDIUM-CHAIN TRIGLYCERIDES; TRISODIUM ETHYLENEDIAMINE DISUCCINATE; SUNFLOWER OIL; COCO-CAPRYLATE; FERRIC OXIDE RED; HYALURONATE SODIUM; CARBOMER INTERPOLYMER TYPE A (ALLYL SUCROSE CROSSLINKED); PANTOTHENIC ACID; PROPANEDIOL; NIACINAMIDE; GLYCERYL STEARATE CITRATE; DIISOPROPYL SEBACATE; LEUCONOSTOC/RADISH ROOT FERMENT FILTRATE; BISMUTH OXYCHLORIDE; MICA; ISODODECANE; GLYCERYL MONOSTEARATE; ETHYLHEXYL HYDROXYSTEARATE; CAPRYLYL GLYCOL; 1,2-HEXANEDIOL; CHLORPHENESIN; BUTYLOCTYL SALICYLATE; LIMONIUM GERBERI WHOLE; COCOA; FERULIC ACID; HYDROXYACETOPHENONE; BUTYLENE GLYCOL; ARGININE; TITANIUM DIOXIDE; POLYMETHYLSILSESQUIOXANE (4.5 MICRONS); TOCOPHEROL; ISODECYL NEOPENTANOATE; ALKYL (C12-15) BENZOATE; WATER; GLYCERIN

Head-to-Toe Favorites Mini Set

Play Everyday Sunscreen SPF 50 with sunflower extract

Active Ingredients Purpose

Avobenzone 3% Sunscreen

Homosalate 10% Sunscreen

Octisalate 5% Sunscreen

Octocrylene 7.5% Sunscreen

Unseen Sunscreen Broad Spectrum SPF 40

Active Ingredients Purpose

Avobenzone 3% Sunscreen

Homosalate 8% Sunscreen

Octocrylene 4% Sunscreen

Octisalate 5% Sunscreen

Glow Screen Body Broad Spectrum SPF 40

Active Ingredient Purpose

Avobenzone 3% Sunscreen

Homosalate 7% Sunscreen

Octisalate 5%. Sunscreen

Octocrylene 10% Sunscreen

Glowscreen SPF 40

Active Ingredients Purpose
Avobenzone 3% Sunscreen
Octisalate 5% Sunscreen
Octocylene 10% Sunscreen

Uses

- Helps Prevent Sunburn
- If used as directed with other sun protection measures (see Directions), decreases the risk of Skin cancer and early skin aging caused by the sun

Keep out of reach of children. If product is swallowed, get medical help or contact a Poison Control Center right away.

Stop use and ask a doctor if rash occurs.

WARNINGS

For external use only

Do not use on damaged or broken skin.

When using this product keep out of eyes. Rinse with water to remove.

Directions

Apply generously and evenly 15 minutes before sun exposure

Reapply at least every 2 hours

Use a water resistant sunscreen if swimming or sweating
Sun Protection Measures: Spending time in the sun increases your risk of skin cancer and early skin aging. To decrease this risk, regularly use a sunscreen with a Broad Spectrum SPF value of 15 or higher and other sun protection measures including:
Limit time in the sun, especially from 10a.m. – 2p.m.

Wear long-sleeved shirts, pants, hats, and sunglasses

Children under 6 months: Ask a doctor

Glow screen body Broad Spectrum SPF 40

- apply generously and evenly 15 minutes before sun exposure
- reapply:
- after 40 minutes of swimming or sweating
- immediately after towel drying
- at least every 2 hours
- Sun Protection Measures Spending time in the sun increases your risk of skin cancer and early skin aging. To decreases this risk, regularly use a sunscreen with a Broad Spectrum SPF value of 15 or higher and other sun protection meausres including: Limit time in the sun, especially from 10 a.m.-2 p.m. Wear long-sleeved shirts, pants, hats, and sunglassess. Children under 6 months: Ask a doctor.

Play Everyday Sunscreen SPF 50 with Sunflower extract

Directions

- Apply liberally 15 minutes before sun exposure

Reapply:

- after 80 minutes of swimming or sweating
- immediately after towel drying
- at least every 2 hours
- Sun Protection Measures. Spending time in the sun increases your risk of skin

cancer and early skin aging. To decrease this risk, regularly use a sunscreen
with broad spectrum SPF of 15 or higher and other sun protection measures
including:

- limit time in the sun, especially from 10 a.m. - 2 p.m.
- Wear Long-sleeved shirts, pants, hats, and sunglasses
- Children under 6 months: Ask a doctor

Play Everyday Sunscreen SPF 50 with sunflower extract

Water, Acrylates Copolymer, Diisopropyl Sebacate, Glycerin, Isodecyl Neopentanoate, Isododecane, Lauryl Lactate, Cetyl Alcohol, Potassium Cetyl Phosphate, Brassica Camprestris/Aleurites Fordi Copolymer, Oryza Sativa (Rice) Bran Extract, Cetearyl Olivate, Ammonium Acryloyldimethyltaurate/VP Copolymer, Hydroxyacetophenone, Sorbitan Olivate, Diethylhexyl Syringylidenemalonate, Aniba Rosaeodora (Rosewood) Wood Oil, Chlorphenesin, Citrus Aurantium Dulcis (Orange) Peel Oil, Citrus Limon (Lemon) Peel Oil, Ethylhexylglycerin, Eucalyptus Globulus Leaf Oil, Ocimum Bascilicum (Basil) Flower/Leaf Extract, Pelargonium Graveolens Flower Oil, Pogostemon Cablin Oil, Pentylene Glycol, 1,2-hexanediol, Caprylyl Glycol, Xanthan Gum, Helianthus Annuus (Sunflower) Extract, Behenic Acid, Cetyl Behenate, Isostearyl Isostearate, Trisodium Ethylenediamene Disuccinate, Tocopherol, Allantoin, Rosmarinus Officinalis (Rosemary) Leaf Extract, Caprylic/Capric Triglyceride,Panthenol, Pentasodium Triphosphate, Citric Acid

Unseen sunscreen SPF 40

Inactive Ingredients

Isododecane, Dimethicone Crosspolymer, Dimethicone/Bis-Isobutyl PPG-20 Crosspolymer, Polymethylsilsesquioxane, Isohexadecane, Dicrapylyl Carbonate, Meadowfoam Estolide, Caprylic/Capric Triglyceride, Polyester-7, Neopentyl Glycol Diheptanoate, Lithothamnion Calcareum Extract,Butyrospermum Parkii (Shea) Butter, Jojoba Esters, Mannitol, Boswellia Serrata Resin Extract, Lecithin, Microcrystalline Cellulose, Diatomaceous Earth, Zinc Sulfate, Silica, Tocopherol

Glow Screen Body Broad Spectrum SPF 40

Aletris Farinosa Root Extract, Bisabolol, Butyloctyl Salicylate,Calcium Sodium Borosilicate, Caprylhydroxamic Acid, Caprylic/Capric Triglyceride, Capryly Glycol, Cetearyl Alcohol, Coco-Caprylate/Caprate, Coco-Glucoside, Coconut Alkanes, Erythritol, Ethyl Ferulate, Ethylhexyl Methoxycrylene, Glycerin, Glyceryl Stearate, Hydrogenated Polycyclopentadiene, Methyl Dlhydroabietate, Mica, Polyester-8, Propanedlol, Sodium Gluconate, Sodium Polyacrylate Starch, Sodium Stearoyl Glutamate, Titanium Dioxide, Tocopherol, Water, Xanthan Gum

Glowscreen SPF 40

Water, Propanediol, Butyloctyl Salicylate, Glycerin, C12-15 Alkyl Benzoate, Polymethylsilsesquioxane, Niacinamide, Glyceryl Stearate Citrate, Bismuth Oxychloride, Mica, Titanium Dioxide, Lauryl Lactate, Isododecane, Isodecyl Neopentanoate, Glyceryl Stearate, Diisopropyl Sebacate, Cetyl Phosphate, Caprylic/Capric Triglyceride, Coco-Caprylate, Ethylhexyl Hydroxystearate, Butylene Glycol, Arginine, Hydroxyacetophenone, Caprylyl Glycol, 1,2-Hexanediol, Iron Oxides, Sodium Hyaluronate, Chlorphenesin, Acrylates/C10-30 Alkyl Acrylate Crosspolymer, Trisodium Ethylenediamine Disuccinate, Phospholipids, Limonium Gerberi Extract, Leuconostoc/Radish Root Ferment Filtrate, Theobroma Cacao (Cocoa) Seed Extract, Pantothenic Acid, Tocopherol, Helianthus Annuus (sunflower) Seed Oil, Ferulic Acid

Head to Toe SPF Favorities Mini Set

Protect your skin from head to toe with this sample set, featuring our favorite glowy and everyday SPFs for face & body.

Unseen Sunscreen SPF 40 (10 ml)

Glowscreen SPF 40 (10ml)

Play Everyday Lotion SPF 50 with sunflower Extract (10ml)

Glowscreen Body SPF 40 (10 ml)

Play Everyday Lotion SPF 50

Supergoop!

PLAY

SPF 50 Everyday Lotion

With Sunflower Extract

Broad Spectrum Sunscreen SPF 50 PA ++++

Water & Sweat Resistant (80 minutes)

0.33 fl. oz./10 ml

Unseen Sunscreen SPF 40

Unseen Sunscreen

SPF 40

Broad Spectrum Sunscreen SPF 40 PA+++

Water & Sweat Resistant (40 minutes)

0.34 fl oz. / 10 ml.

Glowscreen Body SPF 40

Glowscreen Body

SPF 40

Broad Spectrum Sunscreen SPF 40 PA+++

Water & Sweat Resistant (40 minutes)

0.34 fl.oz. / 10ml.

Glowscreen SPF 40

Glowscreen

SPF 40 PA +++

0.34 fl. oz. / 10ml